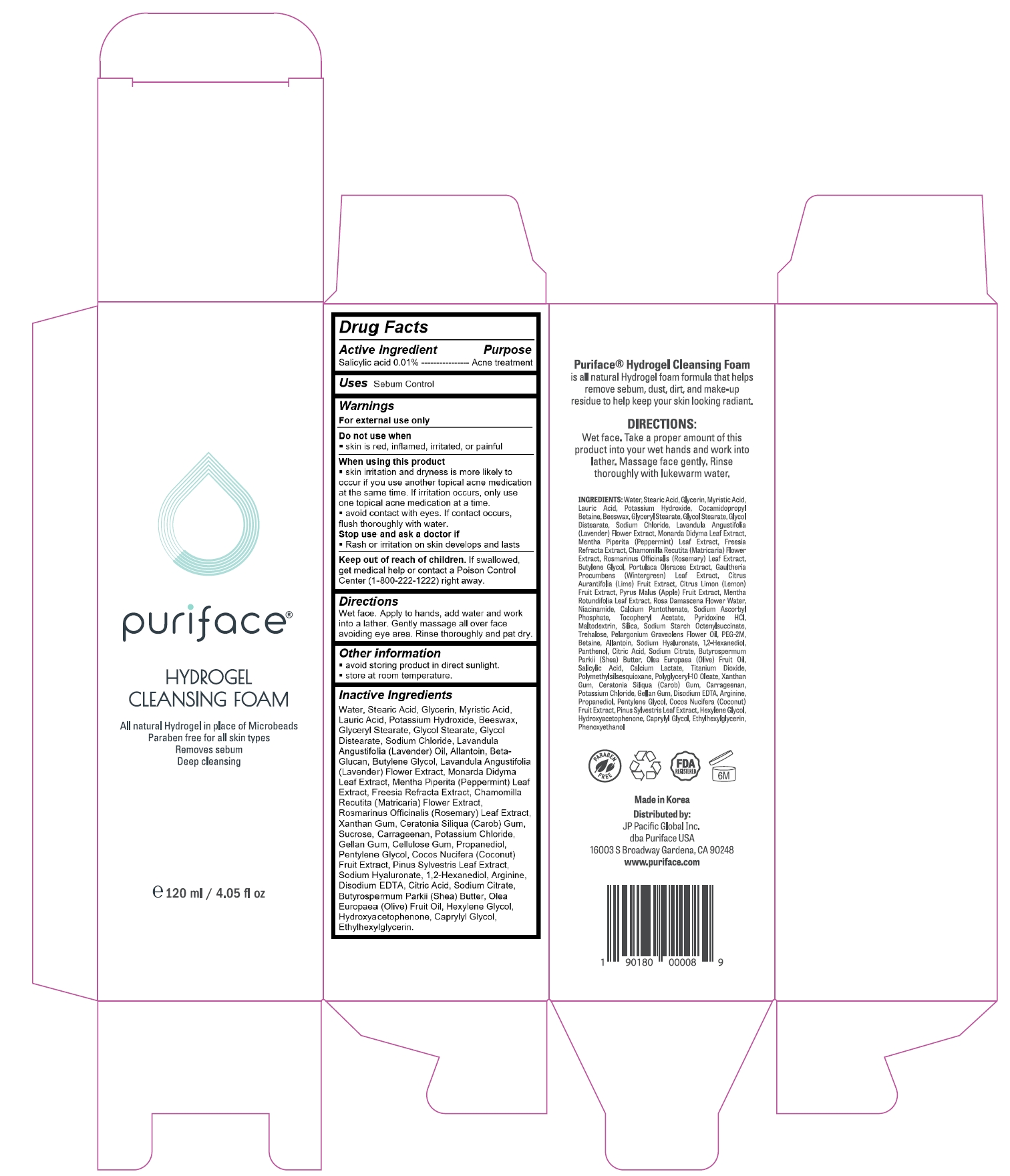 DRUG LABEL: Puriface Hydrogel Cleansing Foam
NDC: 71727-105 | Form: GEL
Manufacturer: iMode Korea, Inc.
Category: otc | Type: HUMAN OTC DRUG LABEL
Date: 20190208

ACTIVE INGREDIENTS: SALICYLIC ACID 0.012 g/120 g
INACTIVE INGREDIENTS: WATER

Puriface Hydrogel Cleansing Foam

Active ingredients

salicylic acid 0.01%

Purpose

Acne Treatment

Uses

Sebum control

Warnings

For external use only

Do not use when

skin is red, inflamed, irritated, or painful

When using this product

§ skin irritation and dryness is more likely to occur if you use another topical acne medication at the same time. If irritation occurs, only use one topical acne medication at a time.

§ avoid contact with eyes. If contact occurs, flush thoroughly with water.

Stop use and ask a doctor if

§ Rash or irritation on skin develops and lasts

Keep out of reach of children. If swallowed, get medical help or contact a Poison Control Center (1-800-222-1222) right away.

Directions

Wet face. Apply to hands, add water and work into a lather. Gently massage all over face avoiding eye area. Rinse thoroughly and pat dry.

Keep out of reach of children

If swallowed, get medical help or contact a Poison Control Center (1-800-222-1222) right away.

Inactive ingredients

Water, Stearic Acid, Glycerin, Myristic Acid, Lauric Acid, Potassium Hydroxide, Beeswax, Glyceryl Stearate, Glycol Stearate, Glycol Distearate, Sodium Chloride, Lavandula Angustifolia (Lavender) Oil, Allantoin, Beta-Glucan, Butylene Glycol, Lavandula Angustifolia (Lavender) Flower Extract, Monarda Didyma Leaf Extract, Mentha Piperita (Peppermint) Leaf Extract, Freesia Refracta Extract, Chamomilla Recutita (Matricaria) Flower Extract, Rosmarinus Officinalis (Rosemary) Leaf Extract, Xanthan Gum, Ceratonia Siliqua (Carob) Gum, Sucrose, Carrageenan, Potassium Chloride, Gellan Gum, Cellulose Gum, Propanediol, Pentylene Glycol, Cocos Nucifera (Coconut) Fruit Extract, Pinus Sylvestris Leaf Extract, Sodium Hyaluronate, 1,2-Hexanediol, Arginine, Disodium EDTA, Citric Acid, Sodium Citrate, Butyrospermum Parkii (Shea) Butter, Olea Europaea (Olive) Fruit Oil, Hexylene Glycol, Hydroxyacetophenone, Caprylyl Glycol, Ethylhexylglycerin.